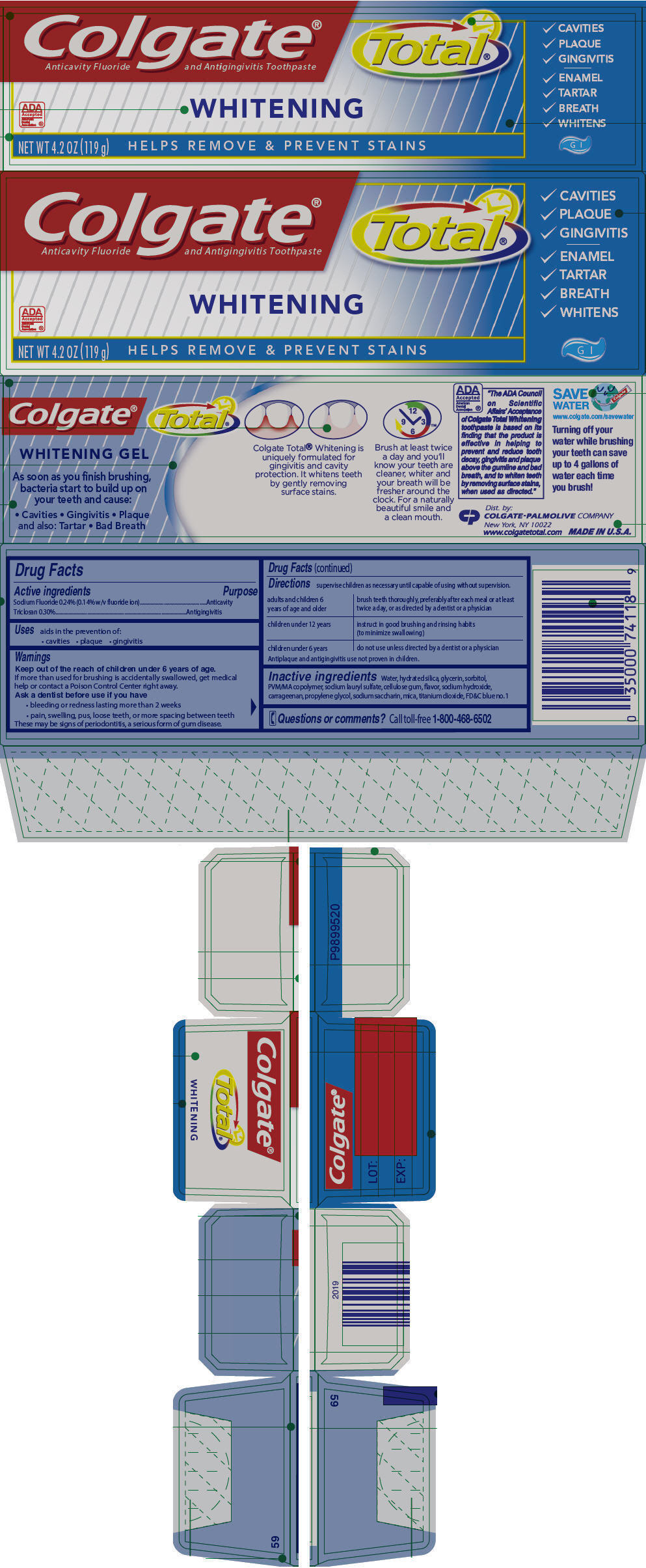 DRUG LABEL: Colgate Total Whitening Gel
NDC: 67659-310 | Form: PASTE, DENTIFRICE
Manufacturer: Team Technologies, Inc
Category: otc | Type: HUMAN OTC DRUG LABEL
Date: 20160520

ACTIVE INGREDIENTS: SODIUM FLUORIDE 1.4 mg/1 g; TRICLOSAN 3 mg/1 g
INACTIVE INGREDIENTS: WATER; HYDRATED SILICA; GLYCERIN; SORBITOL; BUTYL ESTER OF METHYL VINYL ETHER/MALEIC ANHYDRIDE COPOLYMER (125000 MW); SODIUM LAURYL SULFATE; SODIUM HYDROXIDE; PROPYLENE GLYCOL; SACCHARIN SODIUM; CARBOXYMETHYLCELLULOSE SODIUM, UNSPECIFIED FORM; MICA; TITANIUM DIOXIDE; CARRAGEENAN; FD&C BLUE NO. 1

Colgate® Total® Whitening Gel

Drug Facts

ACTIVE INGREDIENT

Active ingredients | Purpose
Sodium Fluoride 0.24% (0.14% w/v fluoride ion) | Anticavity
Triclosan 0.30% | Antigingivitis

Uses

aids in the prevention of:

- cavities
- plaque
- gingivitis

Warnings

KEEP OUT OF REACH OF CHILDREN

Keep out of the reach of children under 6 years of age.

If more than used for brushing is accidentally swallowed, get medical help or contact a Poison Control Center right away.

Ask a dentist before use if you have

- bleeding or redness lasting more than 2 weeks
- pain, swelling, pus, loose teeth, or more spacing between teeth

These may be signs of periodontitis, a serious form of gumdisease.

Directions

supervise children as necessary until capable of using without supervision.

adults and children 6 years of age and older | brush teeth thoroughly, preferably after each meal or at least twice a day, or as directed by a dentist or a physician
children under 12 years | instruct in good brushing and rinsing habits (to minimize swallowing)
children under 6 years | do not use unless directed by a dentist or a physician

Antiplaque and antigingivitis use not proven in children.

Inactive ingredients

Water, hydrated silica, glycerin, sorbitol, PVM/MA copolymer, sodium lauryl sulfate, cellulose gum, flavor, sodium hydroxide, carrageenan, propylene glycol, sodium saccharin, mica, titanium dioxide, FD&C blue no. 1

Questions or comments?

Call toll-free 1-800-468-6502

Dist. by:
COLGATE-PALMOLIVE COMPANY
New York, NY 10022

PRINCIPAL DISPLAY PANEL - 119 g Tube Carton

Colgate®
Anticavity Fluoride and Antigingivitis Toothpaste

Total®

ADA
Accepted
American
Dental
Association ®

WHITENING

NET WT 4.2 OZ (119 g)

HELPS REMOVE & PREVENT STAINS

- CAVITIES
- PLAQUE
- GINGIVITIS
- ENAMEL
- TARTAR
- BREATH
- WHITENS
  G l